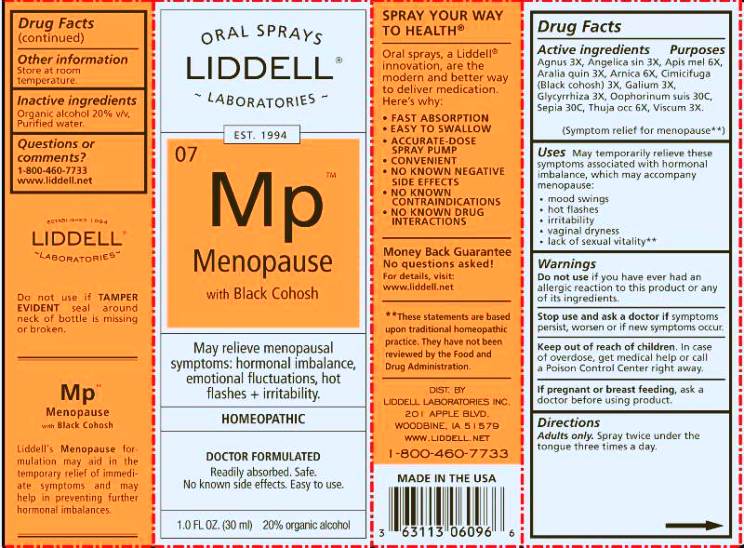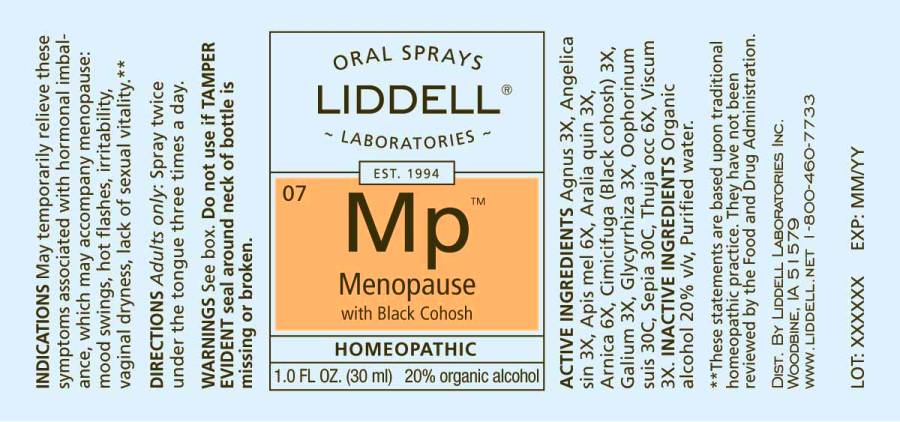 DRUG LABEL: Menopause
NDC: 50845-0092 | Form: LIQUID
Manufacturer: Liddell Laboratories, Inc.
Category: homeopathic | Type: HUMAN OTC DRUG LABEL
Date: 20240701

ACTIVE INGREDIENTS: CHASTE TREE 3 [hp_X]/1 mL; ANGELICA SINENSIS ROOT 3 [hp_X]/1 mL; APIS MELLIFERA 6 [hp_X]/1 mL; AMERICAN GINSENG 3 [hp_X]/1 mL; ARNICA MONTANA WHOLE 6 [hp_X]/1 mL; BLACK COHOSH 3 [hp_X]/1 mL; GALIUM APARINE WHOLE 3 [hp_X]/1 mL; GLYCYRRHIZA GLABRA 3 [hp_X]/1 mL; SUS SCROFA OVARY 30 [hp_C]/1 mL; SEPIA OFFICINALIS JUICE 30 [hp_X]/1 mL; THUJA OCCIDENTALIS LEAFY TWIG 6 [hp_X]/1 mL; VISCUM ALBUM FRUITING TOP 3 [hp_X]/1 mL
INACTIVE INGREDIENTS: WATER; ALCOHOL

DRUG FACTS:

ACTIVE INGREDIENTS:

Agnus castus 3X, Angelica sinensis radix 3X, Apis mellifica 6X, Aralia quinquefolia 3X, Arnica montana 6X, Cimicifuga racemosa 3X, Galium aparine 3X, Glycyrrhiza glabra 3X, Oophorinum suis 30C, Sepia 30C, Thuja occidentalis 6X, Viscum album 3X.

USES:

May temporarily relieve these symptoms associated with hormonal imbalance, which may accompany menopause:

•mood swings

•hot flashes

•irritability

•vaginal dryness

•lack of sexual vitality **

**These statements are based upon traditional homeopathic practice. They have not been reviewed by the Food and Drug Administration.

WARNINGS:

Do not use if you have ever had an allergic reaction to this product or any of its ingredients.

Stop use and ask a doctor if symptoms persist, worsen or if new symptoms occur.

Keep out of reach of children. In case of overdose, get medical help or call a Poison Control Center right away.

If pregnant or breast feeding, ask a doctor before using product.

Do not use if TAMPER EVIDENT seal around neck of bottle is missing or broken.

Other information. Store at room temperature.

Keep out of reach of children. In case of overdose, get medical help or call a Poison Control Center right away.

DIRECTIONS:

Adults only: Spray twice under the tongue three times a day.

INDICATIONS:

May temporarily relieve these symptoms associated with hormonal imbalance, which may accompany menopause:

•mood swings

•hot flashes

•irritability

•vaginal dryness

•lack of sexual vitality **

**These statements are based upon traditional homeopathic practice. They have not been reviewed by the Food and Drug Administration.

INACTIVE INGREDIENTS:

Organic alcohol 20% v/v, Purified water.

QUESTIONS:

DIST. BY

LIDDELL LABORATORIES, INC.

201 APPLE BLVD.

WOODBINE, IA 51579

WWW.LIDDELL.NET

1-800-460-7733

PACKAGE LABEL DISPLAY:

ORAL SPRAYS

LIDDELL LABORATORIES
EST. 1994

^07 MP

Menopause
with Black Cohosh

May relieve menopausal symptoms: hormonal imbalance, emotional fluctuations, hot flashes + irritability.

HOMEOPATHIC

DOCTOR FORMULATED

Readily absorbed. Safe. No known side effects. Easy to use.

1.0 FL OZ (30 ml)